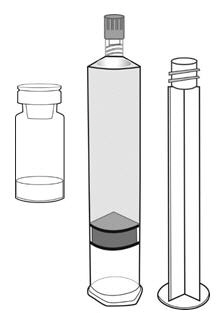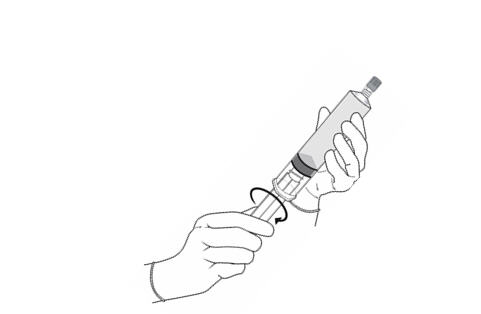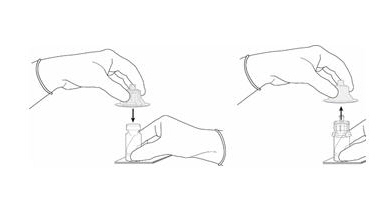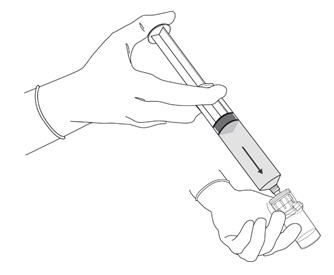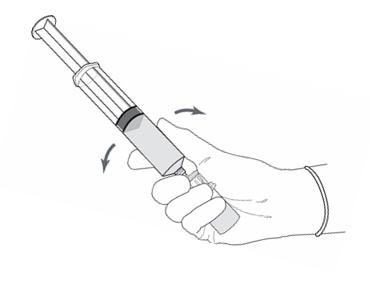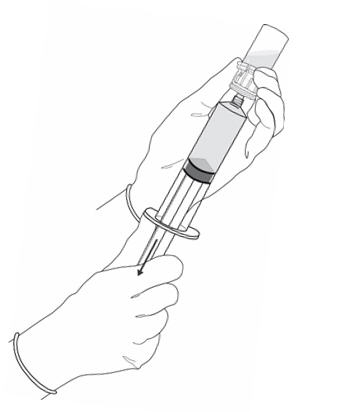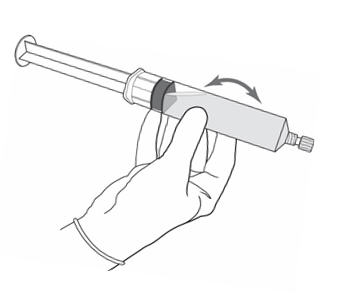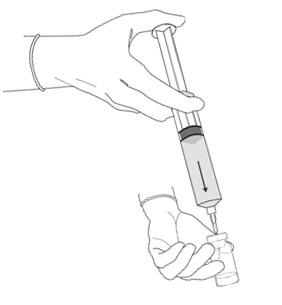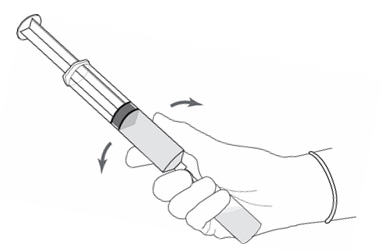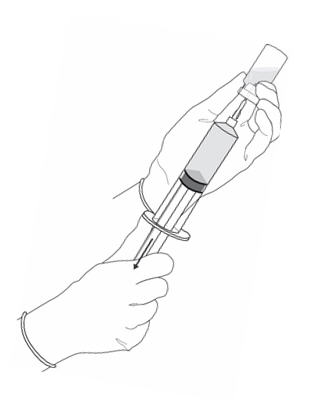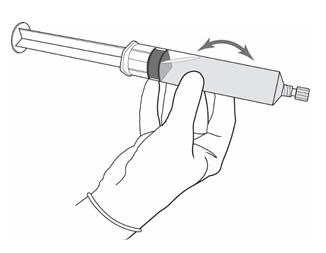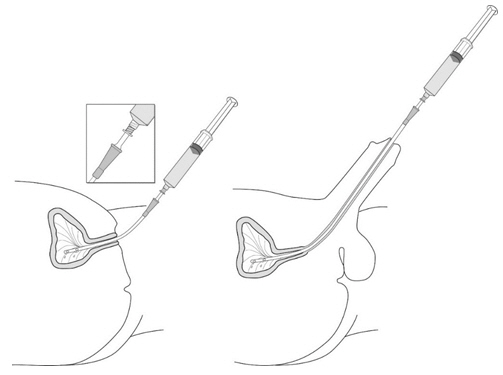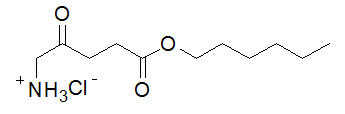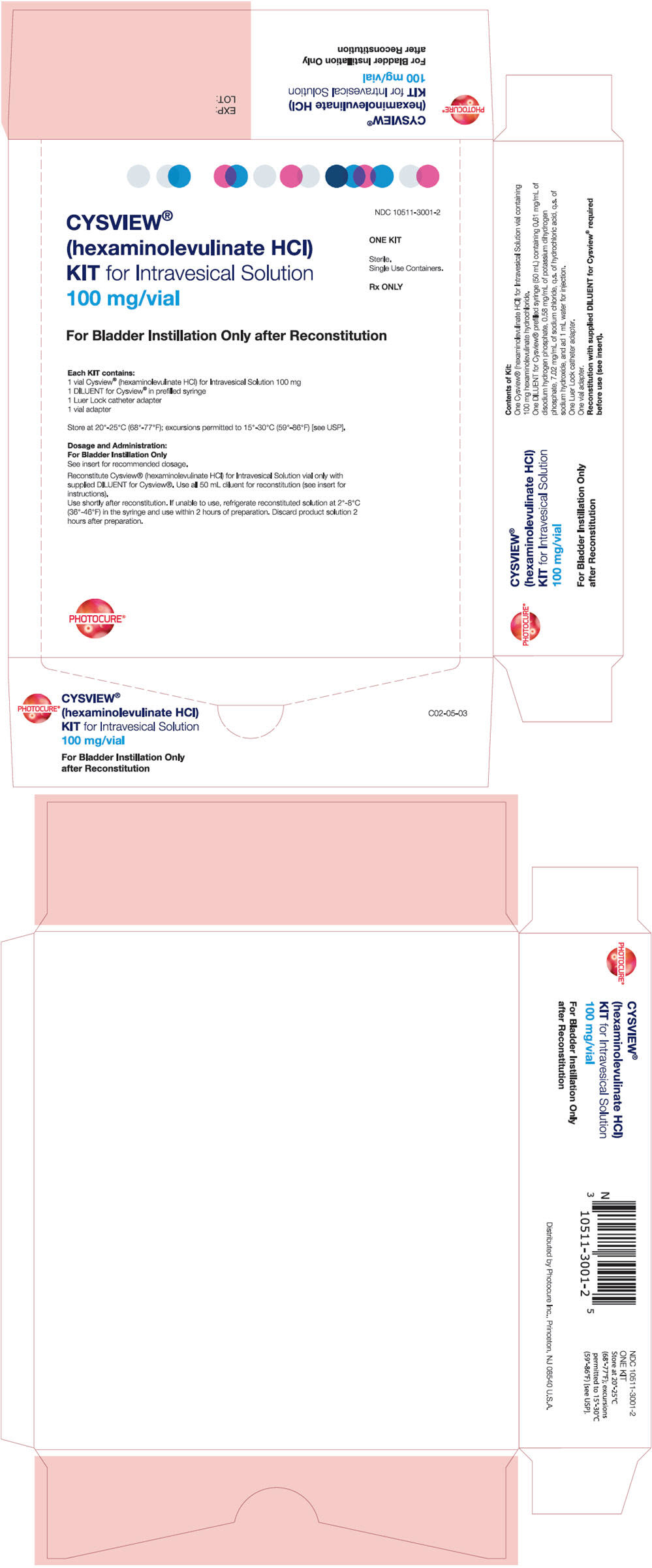 DRUG LABEL: Cysview
NDC: 10511-3001 | Form: KIT | Route: INTRAVESICAL
Manufacturer: Photocure Inc.
Category: prescription | Type: HUMAN PRESCRIPTION DRUG LABEL
Date: 20251205

ACTIVE INGREDIENTS: HEXAMINOLEVULINATE HYDROCHLORIDE 100 mg/50 mL
INACTIVE INGREDIENTS: WATER; SODIUM PHOSPHATE, DIBASIC, DIHYDRATE; MONOBASIC POTASSIUM PHOSPHATE; SODIUM CHLORIDE; HYDROCHLORIC ACID; SODIUM HYDROXIDE

HIGHLIGHTS OF PRESCRIBING INFORMATION

These highlights do not include all the information needed to use Cysview safely and effectively. See full prescribing information for Cysview.
Cysview (hexaminolevulinate hydrochloride), for Intravesical Solution For bladder instillation only
Initial U.S. Approval: 2010

1 INDICATIONS AND USAGE

Cysview is an optical imaging agent indicated for use in the cystoscopic detection of carcinoma of the bladder, including carcinoma in situ (CIS), among patients suspected or known to have lesion(s) on the basis of a prior cystoscopy, or in patients undergoing surveillance cystoscopy for carcinoma of the bladder. Cysview is used with the Karl Storz D-Light C Photodynamic Diagnostic (PDD) system to perform Blue Light Cystoscopy (BLC®) as an adjunct to the white light cystoscopy.

Important Limitations of Use:

- Not a replacement for random bladder biopsies or other procedures used in the detection of bladder cancer. (1.1, 5.2)

2 DOSAGE AND ADMINISTRATION

Training in blue light cystoscopy with the Karl Storz D-Light C PDD system is essential prior to the use of Cysview. (2.5)

- Reconstitute Cysview powder with the supplied 50 mL DILUENT under aseptic conditions. (2.2)
- Use solution of Cysview shortly after reconstitution. If unable to use, the solution may be stored for up to 2 hours in a refrigerator at 2°-8°C (36°-46°F) in the labeled syringe. Discard after 2 hours. (2.2, 16)
- Instill 50 mL of reconstituted solution of Cysview into the emptied bladder via an intravesical catheter. Retain in the bladder for 1 hour before evacuating and performing cystoscopic examination. (2.3, 2.5)
- First perform a complete cystoscopic examination of the entire bladder under white light and then repeat the examination of the entire bladder under blue light. Record and document information about location and appearance of suspicious lesions and areas seen under both white and blue light. (2.5)

3 DOSAGE FORMS AND STRENGTHS

Cysview (hexaminolevulinate hydrochloride) is supplied as a kit. The kit may be supplied as two options; with or without a vial adapter:

- One 10 mL glass vial containing 100 mg powder of Cysview. (hexaminolevulinate hydrochloride) for Intravesical Solution.
- One plastic prefilled syringe containing 50 mL DILUENT for Cysview.
- One Luer Lock catheter adapter.
- One vial adapter for use during reconstitution (in the kit containing the vial adapter). (16)

Once reconstituted, the solution contains 2 mg/mL (8 mmol/L) of hexaminolevulinate hydrochloride.

4 CONTRAINDICATIONS

Do not use Cysview in patients with:

- porphyria,
- gross hematuria,
- known hypersensitivity to hexaminolevulinate or aminolevulinate derivatives. (4)

5 WARNINGS AND PRECAUTIONS

- Anaphylaxis: have trained personnel and therapies available. (5.1).
- Failed Detection: Cysview may not detect all malignant lesions. Always perform white light cystoscopy followed by blue light cystoscopy. Do not biopsy with blue light only. (5.2)
- False fluorescence may occur due to inflammation, cystoscopic trauma, scar tissue, previous bladder biopsy, recent BCG therapy or chemotherapy. (5.3)

6 ADVERSE REACTIONS

The most common adverse reaction reported in patients who received Cysview was bladder spasm, occurring in 2% of patients, followed by dysuria, hematuria and bladder pain. (6.1)

To report SUSPECTED ADVERSE REACTIONS, contact Photocure Inc. at 1-855-297-8439 or FDA at 1-800-FDA-1088 or www.fda.gov/medwatch.

8 USE IN SPECIFIC POPULATIONS

Pediatric Use: Safety and effectiveness in pediatric patients have not been established. (8.4)

FULL PRESCRIBING INFORMATION

1 INDICATIONS AND USAGE

Cysview is indicated for use in the cystoscopic detection of carcinoma of the bladder, including carcinoma in situ (CIS), among patients suspected or known to have lesion(s) on the basis of a prior cystoscopy, or in patients undergoing surveillance cystoscopy for carcinoma of the bladder. Cysview is used with the Karl Storz D-Light C Photodynamic Diagnostic (PDD) system to perform Blue Light Cystoscopy (BLC®) as an adjunct to the white light cystoscopy.

1.1 Limitations of Use

Cysview is not a replacement for random bladder biopsies or other procedures used in the detection of bladder cancer [ see Warnings and Precautions (5.2)].

2 DOSAGE AND ADMINISTRATION

2.1 Recommended Dose

The recommended dose for adults is 50 mL of reconstituted solution of Cysview [ see Dosage and Administration (2.2)], instilled into the bladder via a urinary catheter [ see Dosage and Administration (2.3)].

2.2 Reconstitution of Cysview

Cysview is supplied as a kit containing: a clear glass vial labeled as Cysview (hexaminolevulinate HCl) for Intravesical Solution containing 100 mg hexaminolevulinate hydrochloride as a powder, a prefilled syringe labeled as DILUENT for Cysview containing 50 mL of the diluent, and a catheter adapter. The kit may be supplied as two options; with or without a vial adapter for use during reconstitution.

Perform all steps under aseptic conditions. Wear gloves during the reconstitution procedure; skin exposure to hexaminolevulinate hydrochloride may increase the risk for sensitization to the drug.

Cysview Powder

Cysview Diluent

Plunger Rod

Figure 1.

Reconstitution Using a Vial Adapter

- Fasten the plunger rod into the rubber stopper of the prefilled syringe by turning the plunger rod clockwise until it stops (Figure 1).

Figure 2.

- Remove the plastic cap from the vial. Remove the TyveK® cover from the vial adapter blister package. Do not remove the vial adapter from the package. Place the Cysview vial on a flat surface. Using the blister package to hold the vial adapter, connect to the vial with a downward vertical motion. The vial adapter snaps onto the vial as the spike penetrates the rubber stopper of the vial. Remove the plastic blister package and discard it. Take care not to touch the exposed end of the vial adapter (Figure 2).

Figure 3.

- Remove the cap from the prefilled syringe and carefully retain it for subsequent reattachment to the syringe. Hold the prefilled syringe upright and carefully press the plunger rod upward to remove air. Connect the syringe to the vial adapter. Inject about 10 mL of the diluent from the prefilled syringe down into the vial. The vial should be about ¾ full (Figure 3).

Figure 4.

- Without disconnecting the vial adapter from the vial, hold the vial and syringe in a firm grip (Figure 4) and gently shake to dissolve the powder in the diluent. The powder normally dissolves almost immediately.

Figure 5.

- Turn the vial upside down and withdraw all of the dissolved solution from the vial back into the syringe (Figure 5).
  Do not inject large amounts of air or diluent when vial is inverted as it may block the venting action of the vial adapter. If this occurs, turn the vial upright and pull back on the plunger rod in the syringe.

Figure 6.

- Disconnect the empty vial with the vial adapter from the syringe tip and discard it. Plug the syringe with the syringe cap (Figure 6). Gently mix the contents of the syringe. The reconstituted solution of Cysview is colorless to pale yellow and clear to slightly opalescent, and free from visible particles.
- Peel off the detachable portion of the syringe label. On the syringe label, add two hours to the present time and write the resulting expiration time and date.

Cysview is now reconstituted and ready for use. The solution of Cysview contains 2 mg/mL of hexaminolevulinate hydrochloride. Instill the reconstituted solution of Cysview into the bladder [ see Bladder instillation of Cysview (2.3)]. If unable to administer the solution shortly after reconstitution, store the solution for up to 2 hours in a refrigerator at 2°-8°C (36°- 46°F) in the labeled syringe. If not used within 2 hours, discard the solution [ see How Supplied/Storage and Handling (16)].

Reconstitution Without the Use of a Vial Adapter

- Fasten the plunger rod into the rubber stopper of the prefilled syringe by turning the plunger rod clockwise until it stops (Figure 1).
  Figure 7.
- Remove the plastic cap from the vial. Remove the cap from the prefilled syringe and carefully retain it for subsequent reattachment to the syringe. Attach a needle to the prefilled syringe. Hold the prefilled syringe upright and carefully press the plunger rod upward to remove air. Penetrate the stopper of the Cysview vial with the needle and inject about 10 mL of the diluent from the prefilled syringe down into the vial. The vial should be about ¾ full (Figure 7).
  Figure 8.
- Without withdrawing the needle from the vial, hold the vial and syringe in a firm grip (Figure 8) and gently shake to dissolve of the powder in the diluent. The powder normally dissolves almost immediately.

Figure 9.

- Turn the vial upside down and withdraw all of the dissolved solution from the vial back into the syringe (Figure 9).

Figure 10.

- Remove the needle from the vial, disconnect the needle from the syringe tip and discard it. Plug the syringe with the syringe cap (Figure 10). Gently mix the contents of the syringe. The reconstituted solution of Cysview is colorless to pale yellow and clear to slightly opalescent, and free from visible particles.
- Peel off the detachable portion of the syringe label. On the syringe label, add two hours to the present time and write the resulting expiration time and date.

Cysview is now reconstituted and ready for use. The solution of Cysview contains 2 mg/mL of hexaminolevulinate hydrochloride. Instill the reconstituted solution of Cysview into the bladder [ see Bladder instillation of Cysview (2.3)]. If unable to administer the solution shortly after reconstitution, store the solution for up to 2 hours in a refrigerator at 2°-8°C (36°- 46°F) in the labeled syringe. If not used within 2 hours, discard the solution [ see How Supplied/Storage and Handling (16)].

2.3 Bladder Instillation of Cysview

For bladder instillation of the solution of Cysview, use straight or intermittent, urethral catheters with a proximal funnel opening that will accommodate the Luer Lock adapter. Use only catheters made of vinyl (uncoated or coated with hydrogel), latex (amber or red), and silicone to instill the reconstituted Cysview. Do not use catheters coated or embedded with silver or antibiotics. In-dwelling bladder catheters (Foley catheters) may be used if the catheters are inserted shortly prior to Cysview administration and are removed following the Cysview instillation.

Use the following steps for bladder instillation of Cysview:

- Using standard sterile catheterization technique, first insert the urethral catheter into the bladder of the patient and use the catheter to completely empty the patient's bladder before instillation of Cysview.

Figure 11.

- To attach the syringe containing the solution of Cysview to the catheter, do the following:
  - Remove the syringe cap from the syringe that contains the reconstituted solution of Cysview.
  - Attach the Luer Lock end of the (provided) catheter adapter to the syringe.
  - Insert the tapered end of the catheter adapter into the funnel opening of the catheter. See Figure 11, with the connection enlarged in the inset.
- Slowly instill the solution of Cysview into the bladder through the catheter (Figure 11), ensuring that the complete volume of the syringe (50 mL) is administered.
- After the solution is instilled, remove the catheter and instruct the patient to retain the solution within the bladder for at least 1 hour; do not exceed 3 hours [ see Cystoscopic examination (2.5)]. Patients may stand, sit and move about during the time period between instillation and start of the cystoscopic procedure.
- Evacuate the solution of Cysview from the bladder as part of routine emptying of the bladder immediately prior to the initiation of the cystoscopic procedure (refer to the Karl Storz D-Light C Photodynamic Diagnostic (PDD) System Manual for further details). Also, the patient may void and completely empty the bladder prior to the procedure.

Avoid skin contact with Cysview. If skin does come in contact with Cysview, wash immediately with soap and water and dry off. After voiding the bladder of Cysview, routinely wash the patient's perineal skin region with soap and water and dry.

2.4 Use of the Karl Storz D-Light C Photodynamic Diagnostic (PDD) System

Cysview imaging requires the use of the Karl Storz D-Light C PDD system, which consists of either:

- a light source, a camera head, a camera control unit, a light cable, and a rigid cystoscope for use with the Rigid PDD Cystoscope System, or
- a light source, a camera control unit, and a flexible video cystoscope for use with the Flexible PDD Video Cystoscope System.

The light source enables both white light cystoscopy and blue light (wavelength 360 – 450 nm) fluorescence cystoscopy. Familiarity with this system is essential before beginning the procedure and before instilling Cysview into the bladder. For system set-up and general information for the safe use of the PDD system, refer to the Karl Storz instruction manual for the PDD system and the instruction manuals for each of the system components. The PDD System is not for use by healthcare providers with green-red color blindness.

2.5 Cystoscopic Examination

Training

Training and proficiency in cystoscopic procedures are essential prior to the use of Cysview. Carefully review the instruction manuals provided with the Karl Storz D-Light C Photodynamic Diagnosis (PDD) System. For additional training in the use of the PDD System, contact the manufacturer's representative.

Preparation for Cystoscopy

Initiate the cystoscopic examination within 30 minutes after evacuation of Cysview from the bladder, but no less than 1 or more than 3 hours after Cysview is instilled in the bladder. If the patient did not retain Cysview in the bladder for 1 hour, allow 1 hour to pass from the instillation of Cysview into the bladder to the start of the cystoscopic examination . The efficacy of Cysview has not been established when the solution was retained for less than 1 hour.

Cystoscopic Examination

Empty the patient's bladder and then fill the bladder with a clear fluid (standard bladder irrigation fluid) in order to distend the bladder wall for cystoscopic visibility. Ensure adequate irrigation during examination of the bladder; blood, urine or floating particles in the bladder may interfere with visualization under both white light and blue light.

First perform a complete cystoscopic examination of the entire bladder under white light and then repeat the examination of the entire bladder surface under blue light unless the white light cystoscopy reveals extensive mucosal inflammation. Do not perform the blue light cystoscopy if the white light cystoscopy reveals wide-spread mucosal inflammation. Abnormalities of the bladder mucosa during blue light cystoscopy are characterized by the detection of red, homogenous and intense fluorescence. The margins of the abnormal lesions are typically well-demarcated and in contrast to the normal urothelium, which appears blue. Register and document (map) the location (as appropriate for the cystoscopy procedure) and appearance (e.g. papillary, flat) of suspicious lesions and abnormalities seen under either white or blue light.

During the cystoscopic examination, be aware that:

- a red fluorescence is expected at the bladder outlet and the prostatic urethra; this fluorescence occurs in normal tissue and is usually less intense and more diffuse than the bladder mucosal fluorescence associated with malignant lesions.
- tangential light may give false fluorescence . To help avoid false fluorescence, hold the endoscope perpendicular and close to the bladder wall with the bladder distended.
- false positive fluorescence may result from scope trauma from a previous cystoscopic examination and/or bladder inflammation [ see Warnings and Precautions (5.3)].
- malignant lesions may not fluoresce following Cysview administration, particularly if the lesions are coated with necrotic tissue. Blue light may fail to detect tumors which have a tendency to be necrotic on the surface, and necrotic cells generally do not fluoresce [ see Warnings and Precautions (5.3)].
- when performing the blue light cystoscopy, avoid prolonged blue light exposure. Studies have not evaluated the potential for adverse effects from blue light. In the controlled clinical trials, the cumulative blue light exposure from bladder evaluation, mapping and resection did not exceed 32 minutes for any procedure [ see Clinical Studies (14)].

For rigid cystoscopy, perform biopsy and/or resection of suspicious lesions by transurethral resection of the bladder (TURB) only after completing white and blue light cystoscopic examinations with bladder mapping. Using standard cystoscopic practices, obtain biopsies of abnormal areas identified during either white or blue light examination and perform resections. Always check for the completeness of the resections under both white light and blue light before finalizing the TURB procedure.

3 DOSAGE FORMS AND STRENGTHS

Cysview (hexaminolevulinate hydrochloride) is supplied as a kit. The kit may be supplied as two options; with or without a vial adapter, and contains:

Cysview kit with a vial adapter

- Cysview (hexaminolevulinate hydrochloride) for Intravesical Solution, 100 mg , as a powder in a 10 mL clear glass vial.
- DILUENT for Cysview, 50 mL, in a plastic prefilled syringe.
- One vial adapter for use during reconstitution.
- One Luer Lock catheter adapter (to connect the syringe containing the reconstituted solution of Cysview to the urethral catheter for bladder instillation of Cysview).

Cysview kit without a vial adapter

- Cysview (hexaminolevulinate hydrochloride) for Intravesical Solution, 100 mg , as a powder in a 10 mL clear glass vial.
- DILUENT for Cysview, 50 mL, in a plastic prefilled syringe.
- One Luer Lock catheter adapter (to connect the syringe containing the reconstituted solution of Cysview to the urethral catheter for bladder instillation of Cysview).

Once reconstituted, the solution of Cysview contains 2 mg/mL of hexaminolevulinate hydrochloride.

4 CONTRAINDICATIONS

Cysview is contraindicated in patients with:

- porphyria,
- gross hematuria,
- known hypersensitivity to hexaminolevulinate or any derivative of aminolevulinic acid.

5 WARNINGS AND PRECAUTIONS

5.1 Anaphylaxis

Anaphylaxis, including anaphylactoid shock, has been reported following administration of Cysview [ see Adverse Reactions (6.2)]. Prior to and during use of the Cysview, have trained personnel and therapies available for the treatment of anaphylaxis.

5.2 Failed Detection

Cysview may fail to detect some bladder tumors, including malignant lesions. Cysview is not a replacement for random biopsies or any other procedure usually performed in the cystoscopic evaluation for cancer. Do not perform cystoscopy with blue light alone as malignant lesions can be missed unless the bladder is initially examined under white light [ see Dosage and Administration (2.5) and Clinical Studies (14)].

5.3 False Positive Fluorescence

Fluorescent areas detected during blue light cystoscopy may not indicate a bladder mucosal lesion. In the controlled clinical studies, approximately 20% of the lesions detected only by blue light cystoscopy showed neither dysplasia nor carcinoma [ see Clinical Studies (14)]. False positive fluorescence may result from inflammation, cystoscopic trauma, scar tissue or bladder mucosal biopsy from a previous cystoscopic examination, and recent BCG immunotherapy or intravesical chemotherapy. In a study of patients treated with recent BCG immunotherapy or intravesical chemotherapy, the rate of false positives with blue light was 55% between 6 weeks to 90 days and 41% after 90 days; the false positive rate was 53% and 33% at the respective time intervals with white light.

The presence of urine and/or blood within the bladder may interfere with the detection of tissue fluorescence. To enhance the diagnostic utility of Cysview with the Karl Storz D-Light C PDD System:

- ensure the bladder is emptied of urine prior to the instillation of fluids at cystoscopy;
- biopsy/resect bladder mucosal lesions only following completion of both white light and blue light rigid cystoscopy;

6 ADVERSE REACTIONS

Anaphylaxis has been reported following exposure to Cysview [ see Warnings and Precautions (5.1)].

6.1 Clinical Study Experience

Because clinical trials are conducted under widely varying conditions, adverse reaction rates observed in the clinical trials of a drug cannot be directly compared to rates in the clinical trials of another drug and may not reflect the rates observed in practice.

In seven clinical trials, safety data were obtained from 1,628 patients, aged 32 to 96 years with a median age of 70 years, all primarily Caucasian and approximately 75% male. All patients were evaluated after a single instillation of 50 mL solution of Cysview, and 103 patients received a repeat administration of Cysview. Of these patients, 170 (10.4%) patients reported at least one adverse reaction. The most common adverse reaction was bladder spasm (reported in 2.0% of the patients) followed by dysuria, hematuria, and bladder pain. No patients experienced anaphylaxis. In the randomized controlled clinical study, adverse reactions were similar in nature and rate between the study drug group and the control group. In a controlled study using Cysview in the surveillance setting, adverse reaction types were similar [ see Clinical Studies (14)].

6.2 Postmarketing Experience

The following adverse reactions have been identified during post-approval use of Cysview. Because these reactions are reported voluntarily from a population of uncertain size, it is not always possible to reliably estimate their frequency or establish a causal relationship to drug exposure.

Anaphylactoid shock, hypersensitivity reactions, bladder pain, cystitis and abnormal urinalysis have been reported during post-marketing use of Cysview.

7 DRUG INTERACTIONS

No specific drug interaction studies have been performed.

8 USE IN SPECIFIC POPULATIONS

8.1 Pregnancy

Risk Summary

There are no available data on Cysview use in pregnant women to inform a drug associated risk of adverse developmental outcomes. Adequate reproductive and developmental toxicity studies in animals have not been performed. Systemic absorption following administration of Cysview is expected to be minimal [see Clinical Pharmacology (12.3)].

The background risk of major birth defects and miscarriage for the indicated populations is unknown. All pregnancies have a background risk of birth defect, loss, or other adverse outcomes. In the U.S. general population, the estimated background risk of major birth defects and miscarriage in clinically recognized pregnancies is 2-4% and 15-20%, respectively.

8.2 Lactation

Risk Summary

There are no data on the presence of hexaminolevulinate in human or animal milk, the effects on a breastfed infant, or the effects on milk production. Systemic absorption following administration of Cysview is expected to be minimal [see Clinical Pharmacology (12.3)]. The lack of clinical data during lactation precludes a clear determination of the risk of Cysview to an infant during lactation; therefore, the development and health benefits of breastfeeding should be considered along with the mother's clinical need for Cysview and any potential adverse effects on the breastfed infant from Cysview or from the underlying maternal condition.

8.4 Pediatric Use

Safety and effectiveness in pediatric patients have not been established.

8.5 Geriatric Use

Of 2127 subjects in clinical studies of Cysview, 67% were 65 years and over. No clinically important differences in safety or efficacy have been observed between older and younger patients in the controlled study.

10 OVERDOSAGE

No adverse events were reported in a dose-finding study conducted among patients whose bladders were instilled with twice the recommended concentration (dose) of solution of Cysview.

11 DESCRIPTION

Cysview contains hexaminolevulinate hydrochloride, an optical imaging drug that in solution form is instilled intravesically for use with photodynamic blue light cystoscopy as an adjunct to white light cystoscopy.

The chemical formula for hexaminolevulinate hydrochloride is C11H21NO3∙HCl. Its molecular weight is 251.76 and it has the following structural formula:

Cysview (hexaminolevulinate hydrochloride) for Intravesical Solution is intended for intravesical administration only after reconstitution with the supplied 50 mL DILUENT. Cysview (hexaminolevulinate hydrochloride) for Intravesical Solution and DILUENT for Cysview are supplied together as a kit.

Cysview (hexaminolevulinate hydrochloride) for Intravesical Solution is supplied as a sterile, non-pyrogenic, freeze-dried, white to off-white or pale yellow, powder containing 100 mg of hexaminolevulinate hydrochloride (equivalent of 85 mg of hexaminolevulinate) in a 10 mL clear glass vial. The DILUENT for Cysview is a sterile, non-pyrogenic solution (pH 6) containing 0.61 mg/ mL disodium hydrogen phosphate, 0.58 mg/mL of potassium dihydrogen phosphate, 7.02 mg/mL of sodium chloride, hydrochloric acid, sodium hydroxide, and water for injection. It is a clear, colorless solution, free from visible particles, and is provided in a 50 mL plastic prefilled syringe.

The reconstituted solution of Cysview contains 2 mg/ml of hexaminolevulinate hydrochloride and is colorless to pale yellow. It is free from visible particles and has a pH between 5.7 and 6.2.

12 CLINICAL PHARMACOLOGY

12.1 Mechanism of Action

Cysview is an ester of the heme precursor, aminolevulinic acid. After bladder instillation, Cysview enters the bladder mucosa and is proposed to enter the intracellular space of mucosal cells where it is used as a precursor in the formation of the photoactive intermediate protoporphyrin IX (PpIX) and other photoactive porphyrins (PAPs). PpIX and PAPs are reported to accumulate preferentially in neoplastic cells as compared to normal urothelium, partly due to altered enzymatic activity in the neoplastic cells. After excitation with light at wavelengths between 360 and 450 nm, PpIX and other PAPs return to a lower energy level by fluorescing, which can be detected and used for cystoscopic detection of lesions. The fluorescence from tumor tissue appears bright red and demarcated, whereas the background normal tissue appears dark blue. Similar processes may occur in inflamed cells.

12.2 Pharmacodynamics

In vitro studies have shown increased porphyrin fluorescence in normal urothelium after exposure to Cysview. In the human bladder, a greater accumulation of porphyrins is proposed in neoplastic or inflamed cells, compared to normal urothelium. After bladder instillation of Cysview for approximately 1 hour and subsequent illumination with blue light at wavelengths 360 – 450nm, the porphyrins will fluoresce red [ see Dosage and Administration (2.5)] .

12.3 Pharmacokinetics

After bladder instillation of [^14C]-labeled Cysview (100 mg) for approximately 1 hour in healthy volunteers, absolute bioavailability of Cysview was 7% (90% confidence interval [CI]: 5%-10%). The [^14C]-labeled substance(s) showed biphasic elimination, with an initial elimination half-life of 39 minutes, followed by a terminal half-life of approximately 76 hours. Whole blood analysis showed no evidence of significant binding of Cysview to erythrocytes. An in vitro study showed that Cysview underwent rapid metabolism in human blood.

13 NONCLINICAL TOXICOLOGY

13.1 Carcinogenesis, Mutagenesis, Impairment of Fertility

No studies in animals have been conducted to evaluate the carcinogenic potential of hexaminolevulinate hydrochloride.

Hexaminolevulinate hydrochloride was not mutagenic in in vitro reverse mutation tests in bacteria, or in chromosome aberration tests in human peripheral blood lymphocytes, and was negative in an in vivo micronucleus test in mice after intravenous injection of doses up to 45 mg/kg in the absence of light activation. Adequate studies have not been performed to evaluate the genetic toxicity of hexaminolevulinate hydrochloride in the presence of light activation.

Adequate reproductive and developmental toxicity studies in animals have not been performed to evaluate the effects of hexaminolevulinate hydrochloride on fertility.

13.2 Animal Toxicology and/or Pharmacology

Dose dependent neurological effects such as tremor, increased motor activity, and increased startle and touch escape responses were observed immediately after dosing at doses ≥ 30 mg/kg (24 times human systemic exposure based on the body surface area, using 10% as the upper level of 90% confidence interval of bioavailability) in a single-dose rat study. The animals recovered to normal status by 60 min after dosing. Adverse neurological effects were also noted in other single- or repeat-dose toxicity studies.

Hexaminolevulinate hydrochloride had moderate to strong potential to cause skin sensitization based on a local lymph node assay in mouse.

14 CLINICAL STUDIES

The safety and efficacy of Cysview when used with photodynamic cystoscopy were studied in two controlled clinical trials.

Study 1: A prospective, multicenter, controlled clinical trial in adult patients with known or suspected bladder cancer who were randomized to either white light (WL) cystoscopy (control group, n = 384) or WL followed by blue light (BL) cystoscopy (study drug group, n = 395). Only the study drug group patients received Cysview by bladder instillation prior to cystoscopy. After bladder evacuation of Cysview, bladder lesion mapping was performed initially using the Karl Storz PDD system in the WL mode followed by lesion mapping in the BL mode. Control group patients underwent only WL cystoscopy with lesion mapping. The average age of the randomized patients was 69 years (range 24 to 96); 78% were male and 94% were Caucasian. All patients had previously undergone cystoscopy.

The main diagnostic efficacy outcome was assessed within the study drug group. This assessment compared lesions detected during an initial cystoscopic examination to their centralized histologic findings (the standard of truth). Following the initial diagnostic cystoscopy, patients within both study groups who had histologically confirmed Ta and/or T1 lesions underwent follow-up WL cystoscopy at 3, 6 and 9 months; these histologic evaluations were based upon the site assessments at both the initial and follow-up cystoscopy.

Diagnostic efficacy assessed the number of patients within the study drug group who had at least one additional Ta or T1 bladder cancer detected only by BL; the proportion of these patients was compared to a proposed threshold proportion of 10%. Within the study drug group, 286 patients had at least one Ta and/or T1 lesion, including 47 patients who had at least one of the lesions detected only by BL (see Table 1).

Table 1: BL Cystoscopic Ta and/or T1 Lesion Detection within the Study Drug Group
Number of patients with any Ta and/or T1 lesion detected with either WL or BL | 286
Number (%) of patients with any Ta and/or T1 lesion detected only with BL | 47 (16%)
p-value [Exact test comparison of the proportion to a threshold value of 10%] | 0.001

Some malignant lesions were detected only by WL or BL (see Table 2).

Table 2: Bladder Tumor Detection within the Study Drug Group by WL and/or BL Cystoscopy
Number of lesions | Detected by Both WL & BL | Detected by WL Only | Detected by BL Only
CIS, n = 66 | 33 | 6 | 27
Ta, n = 580 | 472 | 52 | 56
T1, n = 95 | 76 | 10 | 9
T2 – T4, n = 47 | 38 | 8 | 1

Among the lesions detected only by BL, 23% were negative for any carcinoma-related pathology, including dysplasia. Among the lesions detected only by WL, 17% were negative for any carcinoma-related pathology, including dysplasia.

Study 2: A prospective, open-label, within-patient controlled clinical trial using BL cystoscopy in the detection of bladder cancer during surveillance cystoscopy. Patients with bladder cancer in follow-up for tumor recurrence (n=304) received Cysview by bladder instillation. The average age of the patients was 69 years (range 35 to 92); 80% were male and 89% were Caucasian. After bladder evacuation of Cysview, a standard WL cystoscopy was performed, followed by BL cystoscopy using the KARL STORZ D-Light C Photodynamic Diagnostic (PDD) System with the Flexible PDD Videoscope System. Suspected malignant lesions were counted and evaluated. Patients with suspected recurrence (n=103), underwent a Cysview instillation followed by WL and BL rigid cystoscopy in the operating room (OR), including lesion mapping, using the KARL STORZ D-Light C PDD System with the Rigid PDD Cystoscope System. The suspicious lesions were biopsied and surgically removed by TURB. Cysview efficacy assessed the proportion of patients with malignancy detected only with blue light cystoscopy and not WL cystoscopy during the surveillance cystoscopic examination. The assessment was performed at patient level, and compared malignancy detected during the surveillance cystoscopic examination to the centralized histologic findings (the standard of truth) obtained in the OR examination.

Table 3 shows patient-level detection of malignancy suspected in cystoscopic surveillance stage that was verified in the OR stage (n=103). Among the 103 patients, 63 patients had malignancy confirmed: 49 patients had malignancy detected by both WL and BL; 1 patient had malignancy detected by WL only; and 13 patients had malignancy detected by BL only [12.6% with 95% CI (7%, 21%), p<0.0001*]. Among these 103 patients, 40 patients had false positive detections: 17 patients had false positive detection by both WL and BL; 3 patients had false positive detection by WL only; and 20 patients had false positive detection by BL only.

Table 3: Patient Level Malignancy Detection Suspected in BL Cystoscopic Surveillance and Verified in the OR
 | Detected by Both WL and BL | Detected by WL only | Detected by BL only | Total
True Positive | 49 | 1 | 13 | 63
False Positive | 17 | 3 | 20 | 40
Total | 66 | 4 | 33 | 103
* Exact test comparison of the proportion to a threshold value of 0.5%

Among 26 patients with confirmed CIS malignancy, 9 patients had CIS malignancy detected by BL only and 17 patients had CIS malignancy detected by both WL and BL.

In the same study, there were 315 lesions detected during the cystoscopy in the OR. Table 4 shows the detection of lesions by type of malignancy.

Table 4: Lesion Detection by Type of Malignancy as Verified in the OR
Malignancy Type |  |  | Detected by Both WL & BL | Detected by WL Only | Detected by BL Only
CIS, n = 43 | 24 | 3 | 16
Ta, n = 94 |  |  | 61 | 9 | 24
T1, n = 10 |  |  | 7 | 0 | 3
T2 – T4, n = 5 |  |  | 5 | 0 | 0
PUNLMP [papillary urothelial neoplasm of low malignant potential] n=3 |  |  | 2 | 0 | 1
False positive n=160 |  |  | 65 | 22 | 73
Total number of lesions | 164 | 34 | 117

16 HOW SUPPLIED/STORAGE AND HANDLING

Cysview is supplied as a kit labeled Cysview (hexaminolevulinate HCl) Kit for Intravesical Solution, 100 mg. The kit may be supplied as two options; with or without a vial adapter, and contains:

Cysview kit with a vial adapter

- Cysview (hexaminolevulinate hydrochloride) for Intravesical Solution, 100 mg, as a powder in a 10 mL clear glass vial.
- One plastic prefilled syringe of DILUENT for Cysview, 50 mL.
- One vial adapter for use during reconstitution. The vial adapter is either a "West Vented Vial Adapter" or a "West Mixject Dispensing Pin".
- One Luer Lock catheter adapter (to connect the syringe containing the reconstituted solution of Cysview to the urethral catheter for bladder instillation of Cysview).

NDC 10511-3001-2

Cysview kit without a vial adapter

- Cysview (hexaminolevulinate hydrochloride) for Intravesical Solution, 100 mg , as a powder in a 10 mL clear glass vial.
- One plastic prefilled syringe of DILUENT for Cysview, 50 mL.
- One Luer Lock catheter adapter (to connect the syringe containing the reconstituted solution of Cysview to the urethral catheter for bladder instillation of Cysview).

NDC 10511-3001-3

Storage

Store Cysview (hexaminolevulinate hydrochloride) Kit for Intravesical Solution at 20°-25°C (68°-77°F); excursions are permitted to 15°-30°C (59°-86°F). Do not use beyond the expiry date printed on the carton.

Use the solution of Cysview shortly after reconstitution. If unable to use within this time period, the reconstituted solution can be stored under refrigeration at 2°-8°C (36°-46°F) for up to 2 hours in the labeled syringe.

17 PATIENT COUNSELING INFORMATION

Ask patients if they have:

- a diagnosis or a family history of porphyria,
- allergy to aminolevulinic acid or prior exposure to Cysview,
- gross hematuria,
- had BCG immunotherapy or chemotherapy within the bladder.

Inform patients that Cysview should be retained in the bladder for 1 hour from instillation of Cysview to the start of the cystoscopic procedure. If the patient cannot hold Cysview for 1 hour but needs to void and expel Cysview from the bladder, he or she may void and should then inform a healthcare professional [ see Dosage and Administration (2)].

Distributed by Photocure Inc. Princeton, NJ 08540 U.S.A.

Cysview and BLC are registered trademarks of Photocure ASA with registration numbers 4021232 and 5461301, respectively.

Photocure and the Photocure logo are registered trademarks of Photocure ASA.
© 2019 Photocure ASA – All rights reserved.

PRINCIPAL DISPLAY PANEL - Kit Carton

CYSVIEW®
(hexaminolevulinate HCl)
KIT for Intravesical Solution
100 mg/vial

NDC 10511-3001-2

ONE KIT

Sterile.
Single Use Containers.

Rx ONLY

For Bladder Instillation Only after Reconstitution

Each KIT contains:
1 vial Cysview® (heaminolevulinate HCl) for Intravesical Solution 100 mg
1 DILUENT for Cysview® in prefilled syringe
1 Luer Lock catheter adapter
1 vial adapter

Store at 20°-25°C (68°-77°F); excursions permitted to 15°-30°C (59°-86°F) [see USP].

Dosage and Administration:
For Bladder Instillation Only

See insert for recommended dosage.

Reconstitute Cysview® (hexaminolevulinate HCl) for Intravesical Solution vial only with
supplied DILUENT for Cysview®. Use all 50 mL diluent for reconstitution (see insert for
instructions).
Use shortly after reconstitution. If unable to use, refrigerate reconstituted solution at 2°-8°C
(36°-46°F) in the syringe and use within 2 hours of preparation. Discard product solution 2
hours after preparation.

PHOTOCURE®